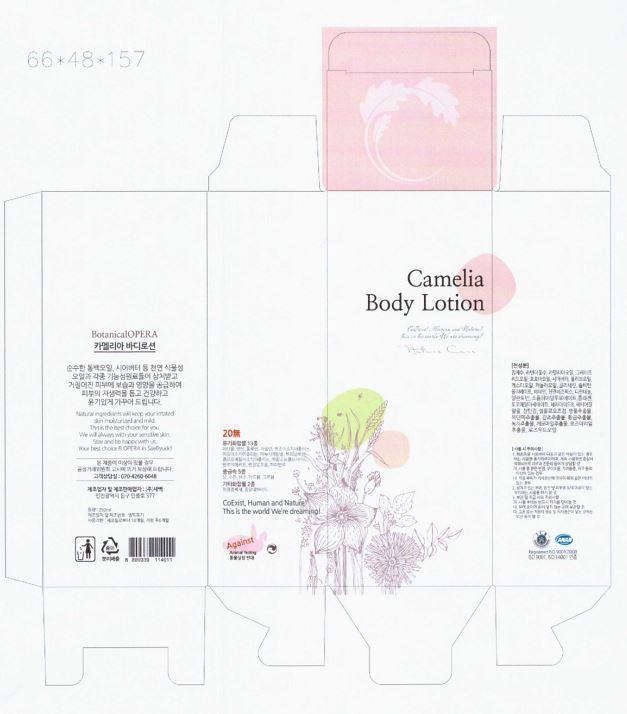 DRUG LABEL: CAMELIA BODY
NDC: 69602-1001 | Form: LOTION
Manufacturer: Saebyuck Corp.
Category: otc | Type: HUMAN OTC DRUG LABEL
Date: 20150308

ACTIVE INGREDIENTS: GLYCERIN 2 g/100 mL
INACTIVE INGREDIENTS: WATER; DEXPANTHENOL; CARBOXYMETHYLCELLULOSE SODIUM

Drug Facts

ACTIVE INGREDIENT

glycerine

INACTIVE INGREDIENT

water, lavender flower water, camellia seed oil, grape seed oil, jojoba seed oil, shea butter, olive fruit oil, castor seed oil, etc

PURPOSE

skin protectant

keep out of reach of the children

INDICATIONS AND USAGE

towel dry your body completely after shower or bath
put an appropriate amount of body lotion onto the palm of your hand and massage lotion gently to the skin

WARNINGS

・Stop using the product when you have skin problems or the product disagrees with your skin
・Stop using the product immediately and consult a dermatologist if you have redness, swelling, itching or irritation on the skin while or after using the product.
・Don't place the product in any place where it will be subjected to extremely high or low temperatures or direct sunlight.

DOSAGE AND ADMINISTRATION

for external use only